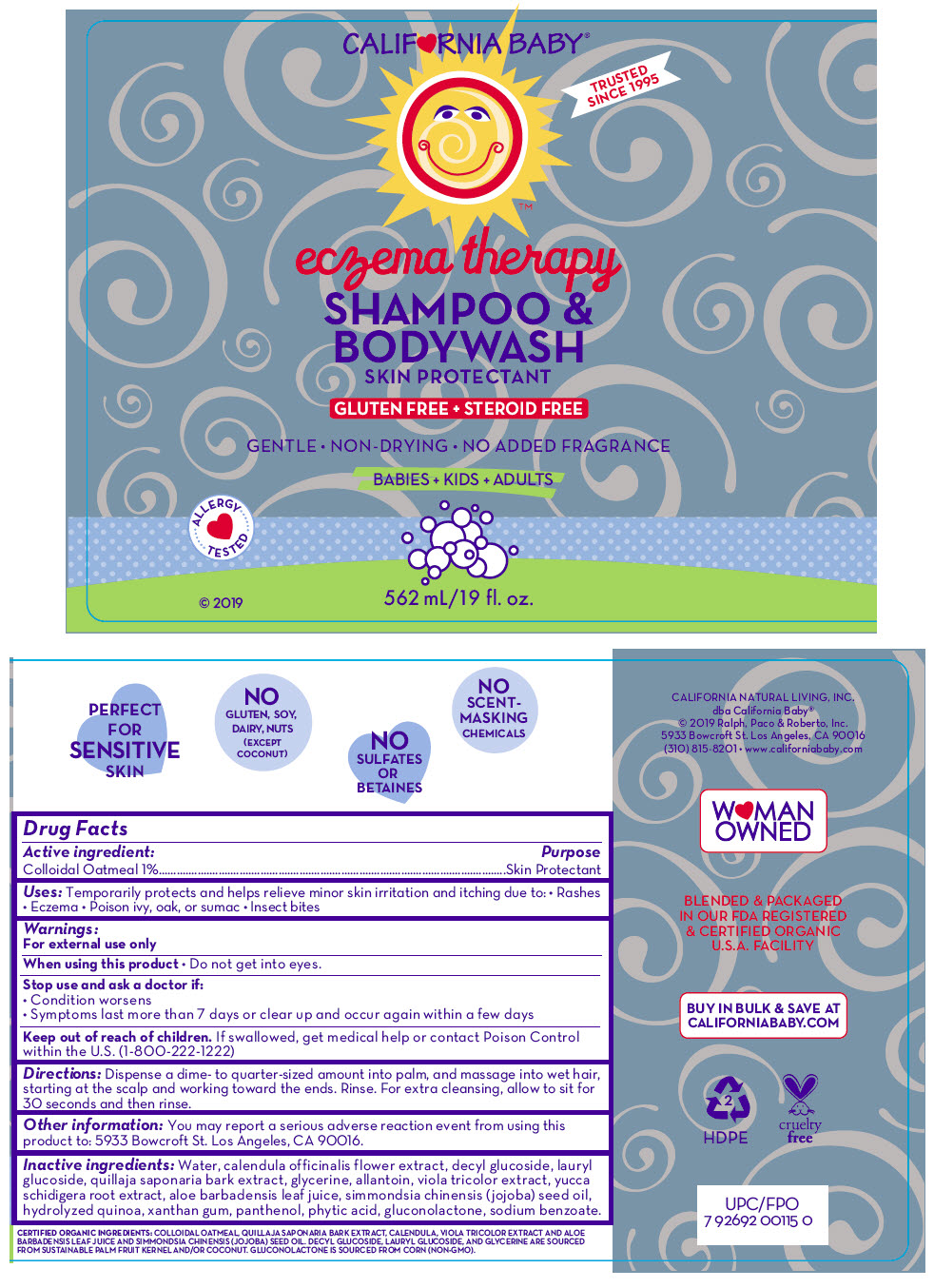 DRUG LABEL: ECZEMA
NDC: 52915-010 | Form: LOTION/SHAMPOO
Manufacturer: ORGANIC & SUSTAINABLE BEAUTY
Category: otc | Type: HUMAN OTC DRUG LABEL
Date: 20241105

ACTIVE INGREDIENTS: OATMEAL 10 mg/1 mL
INACTIVE INGREDIENTS: Water; decyl glucoside; lauryl glucoside; quillaja saponaria bark; glycerin; allantoin; calendula officinalis flower; VIOLA TRICOLOR WHOLE; yucca schidigera root; aloe vera leaf; jojoba oil; quinoa oil; xanthan gum; panthenol; fytic acid; gluconolactone; sodium benzoate

ECZEMA SHAMPOO & BODYWASH

Drug Facts

Active ingredient

Colloidal Oatmeal 1%

Purpose

Skin Protectant

Uses

Temporarily protects and helps relieve minor skin irritation and itching due to:

- Rashes
- Eczema
- Poison ivy, oak, or sumac
- Insect bites

Warnings

External use only.

When using this product

- patch test before use
- keep out of eyes
- clean with soap and water to remove
- to avoid slipping, use mat in tub or shower

Stop use and ask a doctor if

- condition worsens
- symptoms last more than 7 days or clear up and occur again within a few days

Keep out of reach of children. If swallowed, get medical help or contact Poison Control within the U.S. (1-800-222-1222)

Directions

- dispense a dime-to-quarter sized amount into palm, massage into wet hair starting at the scalp and working to the ends. Rinse.
- for extra cleansing, allow to sit for 30 seconds and then rinse.

Other information

You may report a serious adverse reaction event from using this product to: 5933 Bowcroft St. Los Angeles, CA 90016

Inactive ingredients

Water, decyl glucoside, lauryl glucoside, quillaja saponaria bark extract, glycerine, allantoin, calendula officinalis flower extract, viola tricolor extract, yucca schidigera root extract, aloe barbadensis leaf juice, simmondsia chinensis (jojoba) seed oil, hydrolyzed quinoa, xanthan gum, panthenol, phytic acid, gluconolactone, sodium benzoate.

PRINCIPAL DISPLAY PANEL - 562 mL Bottle Label

CALIF♥RNIA BABY®

TRUSTED
SINCE 1995

eczema therapy

SHAMPOO &
BODYWASH
SKIN PROTECTANT

GLUTEN FREE + STEROID FREE

GENTLE • NON-DRYING • NO ADDED FRAGRANCE

BABIES + KIDS + ADULTS

ALLERGY
TESTED

© 2019

562 mL/19 fl. oz.